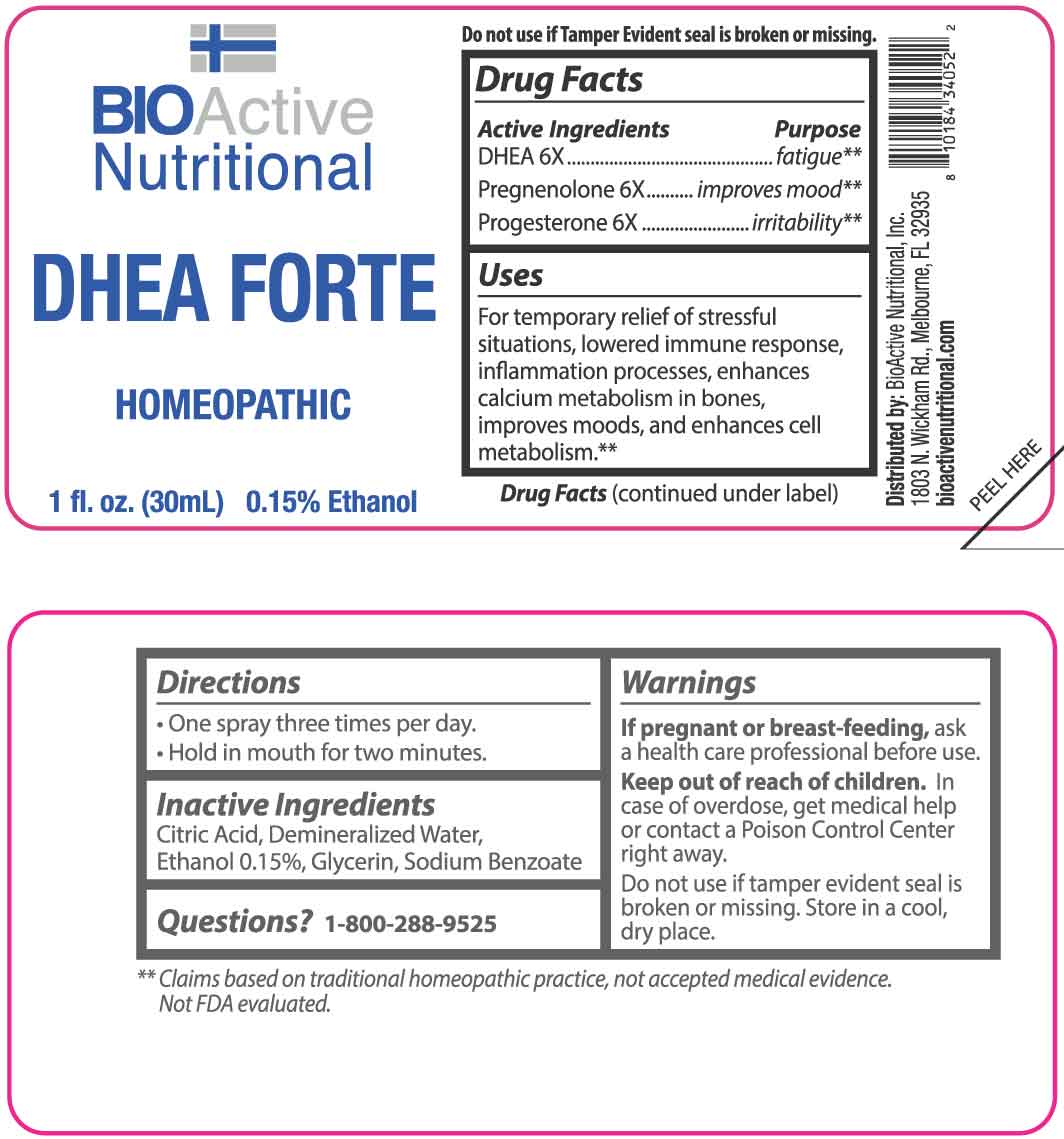 DRUG LABEL: DHEA Forte
NDC: 43857-0052 | Form: LIQUID
Manufacturer: BioActive Nutritionals, Inc.
Category: homeopathic | Type: HUMAN OTC DRUG LABEL
Date: 20251211

ACTIVE INGREDIENTS: PRASTERONE 6 [hp_X]/1 mL; PREGNENOLONE 6 [hp_X]/1 mL; PROGESTERONE 6 [hp_X]/1 mL
INACTIVE INGREDIENTS: GLYCERIN; SODIUM BENZOATE; CITRIC ACID MONOHYDRATE; WATER

DRUG FACTS:

ACTIVE INGREDIENTS:

DHEA 6X, Pregnenolone 6X, Progesterone 6X.

PURPOSE:

DHEA - fatigue,** Pregnenolone – improves mood,** Progesterone – irritability**

**Claims based on traditional homeopathic practices, not accepted medical evidence. Not FDA evaluated.

USES:

For temporary relief of stressful situations, lowered immune response, inflammation processes, enhances calcium metabolism in bones, improves moods, and enhances cell metabolism.**

**Claims based on traditional homeopathic practices, not accepted medical evidence. Not FDA evaluated.

WARNINGS:

If pregnant or breast-feeding, ask a health care professional before use.

Keep out of reach of children. In case of overdose, get medical help or contact a Poison Control Center right away.

Do not use if tamper evident seal is broken or missing.

Store in a cool, dry place.

KEEP OUT OF REACH OF CHILDREN:

In case of overdose, get medical help or contact a Poison Control Center right away.

DIRECTIONS:

• One spray three times per day.

Hold in mouth for two minutes.

INACTIVE INGREDIENTS:

Citric Acid, Demineralized Water, Ethanol 0.15%, Glycerin, Sodium Benzoate

QUESTIONS:

Distributed by:
BioActive Nutritional, Inc.
1803 N. Wickham Rd.
Melbourne, FL 32935
bioactivenutritional.com

1-800-288-9525

PACKAGE LABEL DISPLAY:

BIOActive Nutritional

DHEA FORTE

HOMEOPATHIC

1 fl. oz. (30 mL)